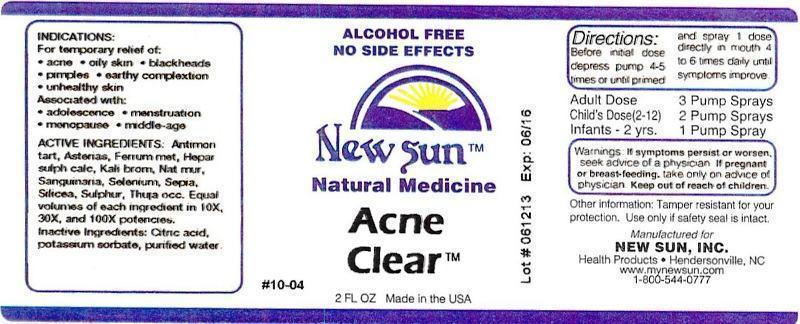 DRUG LABEL: Acne Clear
NDC: 66579-0010 | Form: LIQUID
Manufacturer: New Sun Inc.
Category: homeopathic | Type: HUMAN OTC DRUG LABEL
Date: 20141020

ACTIVE INGREDIENTS: ANTIMONY POTASSIUM TARTRATE 10 [hp_X]/59 mL; ASTERIAS RUBENS 10 [hp_X]/59 mL; IRON 10 [hp_X]/59 mL; CALCIUM SULFIDE 10 [hp_X]/59 mL; POTASSIUM BROMIDE 10 [hp_X]/59 mL; SODIUM CHLORIDE 10 [hp_X]/59 mL; SANGUINARIA CANADENSIS ROOT 10 [hp_X]/59 mL; SELENIUM 10 [hp_X]/59 mL; SEPIA OFFICINALIS JUICE 10 [hp_X]/59 mL; SILICON DIOXIDE 10 [hp_X]/59 mL; SULFUR 10 [hp_X]/59 mL; THUJA OCCIDENTALIS LEAFY TWIG 10 [hp_X]/59 mL
INACTIVE INGREDIENTS: WATER; CITRIC ACID MONOHYDRATE; POTASSIUM SORBATE

Acne Clear

DOSAGE AND ADMINISTRATION

Directions: Before initial dose depress pump 4-5 times or until primed and spray 1 dose directly in mouth 4 to 6 times daily until symptoms improve.

Adult Dose: 3 Pump Sprays

Child's Dose (2-12): 2 Pump Sprays

Infants - 2 yrs: 1 Pump Spray

WARNINGS

Warnings: If symptoms persist or worsen, seek advice of a physician. If pregnant or breast-feeding, take only on advice of physician.

Keep out of reach of children.

Other information: Tamper resistant for your protection. Use only if safety seal is intact.

PURPOSE

Indications: For temporary relief of: •acne •oily skin •blackheads •pimples •earthy complextion •unhealthy skin

Associated with: •adolescence •menstruation •menopause •middle-age

ACTIVE INGREDIENT

Active Ingredients: Antimonium tartaricum, Asterias rubens, Ferrum metallicum, Hepar sulphuris calcareum, Kali bromatum, Natrum muriaticum, Sanguinaria canadensis, Selenium metallicum, Sepia, Silicea, Sulphur, Thuja occidentalis. Equal volumes of each ingredient in 10X, 30X, 100X potencies.

Inactive Ingredient: Citric acid, potassium sorbate, purified water.

Indications: For temporary relief of:

- acne
- oily skin
- blackheads
- pimples
- earthy complextion
- unhealthy skin

Associated with:

- adolescence
- menstruation
- menopause
- middle-age